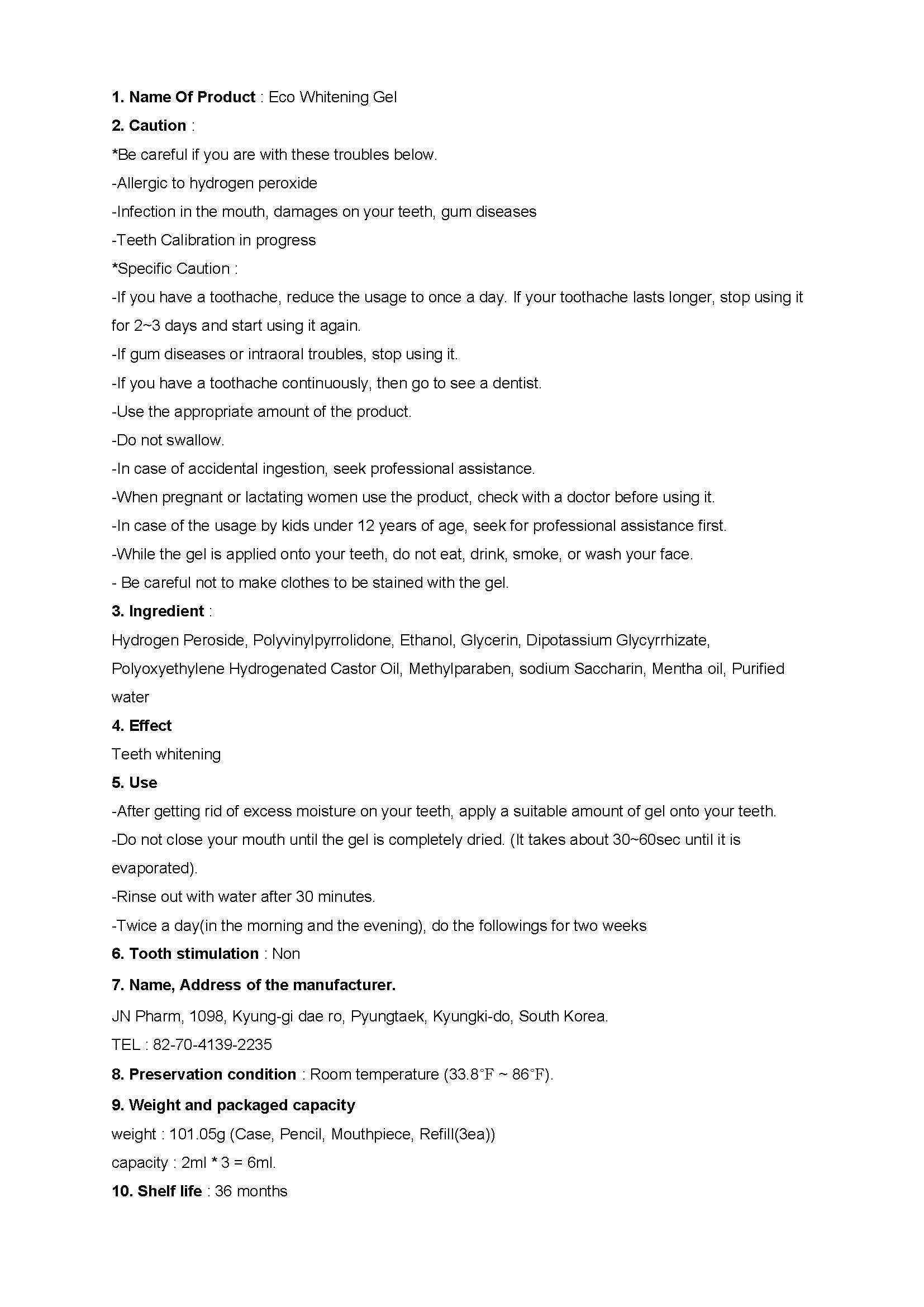 DRUG LABEL: Eco Whitening
NDC: 62040-1001 | Form: GEL
Manufacturer: JN Pharm
Category: otc | Type: HUMAN OTC DRUG LABEL
Date: 20140208

ACTIVE INGREDIENTS: HYDROGEN PEROXIDE 8.57 g/100 mL
INACTIVE INGREDIENTS: WATER; GLYCERIN; GLYCYRRHIZINATE DIPOTASSIUM

Drug Facts

ACTIVE INGREDIENT

Hydrogen Peroxide

INACTIVE INGREDIENT

Polyvinylpyrrolidone, Ethanol, Glycerin, Dipotassium Glycyrrhizate, Polyoxyethylene Hydrogenated Castor Oil, Methylparaben, sodium Saccharin, Mentha oil, Purified water

PURPOSE

teeth whitening

keep out or reach of the children

INDICATIONS AND USAGE

-After getting rid of excess moisture on your teeth, apply a suitable amount of gel onto your teeth.
-Do not close your mouth until the gel is completely dried. (It takes about 30~60sec until it is evaporated).
-Rinse out with water after 30 minutes.
-Twice a day(in the morning and the evening), do the followings for two weeks

WARNINGS

*Be careful if you are with these troubles below.
-Allergic to hydrogen peroxide
-Infection in the mouth, damages on your teeth, gum diseases
-Teeth Calibration in progress
*Specific Caution :
-If you have a toothache, reduce the usage to once a day. If your toothache lasts longer, stop using it for 2~3 days and start using it again.
-If gum diseases or intraoral troubles, stop using it.
-If you have a toothache continuously, then go to see a dentist.
-Use the appropriate amount of the product.
-Do not swallow.
-In case of accidental ingestion, seek professional assistance.
-When pregnant or lactating women use the product, check with a doctor before using it.
-In case of the usage by kids under 12 years of age, seek for professional assistance first.
-While the gel is applied onto your teeth, do not eat, drink, smoke, or wash your face.
- Be careful not to make clothes to be stained with the gel.

DOSAGE AND ADMINISTRATION

dental use only